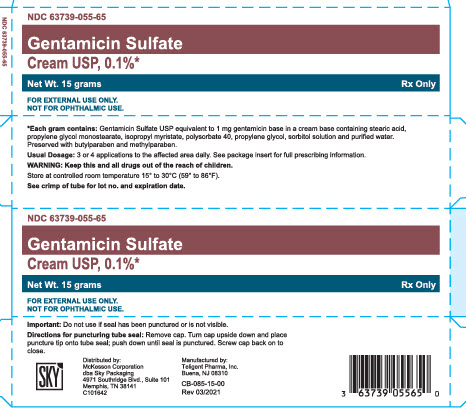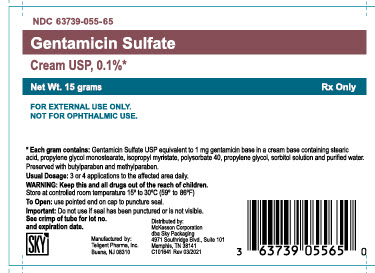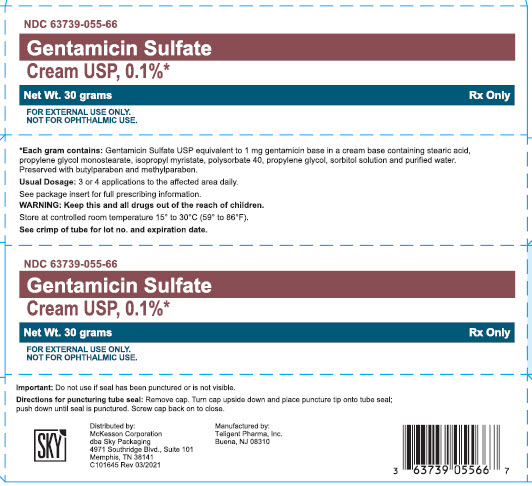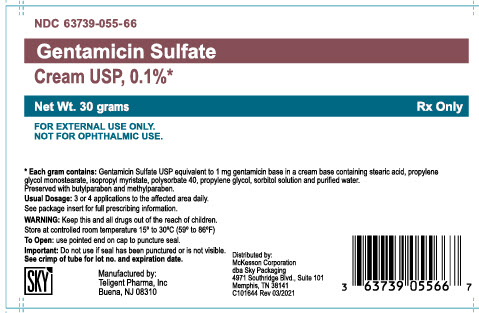 DRUG LABEL: Gentamicin Sulfate Cream USP, 0.1%
NDC: 63739-055 | Form: CREAM
Manufacturer: McKesson Corporation
Category: prescription | Type: HUMAN PRESCRIPTION DRUG LABEL
Date: 20210525

ACTIVE INGREDIENTS: Gentamicin Sulfate 1 mg/1 g
INACTIVE INGREDIENTS: Stearic Acid; Propylene Glycol Monopalmitostearate; Isopropyl Myristate; Polysorbate 40; Propylene Glycol; Sorbitol; Water; Methylparaben; Butylparaben

Gentamicin Sulfate Cream USP, 0.1%

DESCRIPTION

Gentamicin Sulfate Cream is a wide spectrum antibiotic preparation for topical administration. Each gram contains Gentamicin Sulfate USP equivalent to 1 mg gentamicin base in a cream base containing stearic acid, propylene glycol monostearate, isopropyl myristate, polysorbate 40, propylene glycol, sorbitol solution and purified water with methylparaben and butylparaben as preservatives.

CLINICAL PHARMACOLOGY

Gentamicin Sulfate is a wide spectrum antibiotic that provides highly effective topical treatment in primary and secondary bacterial infections of the skin. Gentamicin Sulfate Cream may clear infections that have not responded to treatment with other topical antibiotic agents. In primary skin infections such as impetigo contagiosa, treatment 3 or 4 times daily with Gentamicin Sulfate Cream usually clears the lesions promptly. In secondary skin infections, Gentamicin Sulfate Cream aids in the treatment of the underlying dermatoses by controlling the infection. Bacteria susceptible to the action of gentamicin sulfate include sensitive strains of Streptococci (group A beta-hemolytic, alpha-hemolytic), Staphylococcus aureus (coagulase positive, coagulase negative, and some penicillinase-producing strains), and the gram-negative bacteria, Pseudomonas aeruginosa, Aerobacter aerogenes, Escherichia coli, Proteus vulgaris, and Klebsiella pneumoniae.

INDICATIONS AND USAGE

Primary skin infections: Impetigo contagiosa, superficial folliculitis, ecthyma, furunculosis, sycosis barbae, and pyoderma gangrenosum. Secondary skin infections: Infectious eczematoid dermatitis, pustular acne, pustular psoriasis, infected seborrheic dermatitis, infected contact dermatitis (including poison ivy), infected excoriations, and bacterial super-infections of fungal or viral infections. Please Note: Gentamicin Sulfate is a bactericidal agent that is not effective against viruses or fungi in skin infections. Gentamicin Sulfate is useful in the treatment of infected skin cysts and certain other skin abscesses when preceded by incision and drainage to permit adequate contact between the antibiotic and the infecting bacteria. Good results have been obtained in the treatment of infected stasis and other skin ulcers, infected superficial burns, paronychia, infected insect bites and stings, infected lacerations and abrasions, and wounds from minor surgery. Patients sensitive to neomycin can be treated with Gentamicin Sulfate, although regular observation of patients sensitive to topical antibiotics is advisable when such patients are treated with any topical antibiotic. Gentamicin Sulfate Cream is recommended for wet, oozing primary infections, and greasy, secondary infections, such as pustular acne or infected seborrheic dermatitis. If a water-washable preparation is desired, the cream is preferable. Gentamicin Sulfate Cream has been used successfully in infants over one year of age, as well as in adults and children.

CONTRAINDICATIONS

This drug product is contraindicated in individuals with a history of sensitivity to any of its components.

PRECAUTIONS

The use of topical antibiotics occasionally allows overgrowth of nonsusceptible organisms, including fungi. If this condition occurs, or if irritation, sensitization or superinfection develops, treatment with gentamicin sulfate should be discontinued and appropriate therapy instituted.

ADVERSE REACTIONS

In patients with dermatoses treated with Gentamicin Sulfate, irritation (erythema and pruritis) that did not usually require discontinuance of treatment has been reported in a small percentage of cases. There was no evidence of irritation or sensitization, however, in any of these patients patch-tested subsequently with Gentamicin Sulfate on normal skin. Possible photosensitization has been reported in several patients but could not be elicited in these patients by reapplication of Gentamicin Sulfate followed by exposure to ultraviolet radiation.

To report SUSPECTED ADVERSE REACTIONS, contact Teligent Pharma, Inc. at 1-856-697-1441, or FDA at 1-800-FDA-1088 or www.fda.gov/medwatch.

DOSAGE AND ADMINISTRATION

A small amount of Gentamicin Sulfate Cream should be applied gently to the lesions three or four times daily. The area treated may be covered with a gauze dressing if desired. In impetigo contagiosa, the crusts should be removed before application of gentamicin sulfate to permit maximum contact between the antibiotic and the infection. Care should be exercised to avoid further contamination of the infected skin. Infected stasis ulcers have responded well to treatment with gentamicin sulfate under gelatin packing.

HOW SUPPLIED

Gentamicin Sulfate Cream USP, 0.1% is supplied as follows:
15 gram tube (NDC 63739-055-65)
30 gram tube (NDC 63739-055-66)

Store at controlled room temperature 15° to 30°C (59° to 86°F).

Manufactured by:
Teligent Pharma, Inc.
Buena, NJ 08310
Distributed by:
McKesson Corporation
dba Sky Packaging
4971 Southridge Blvd., Suite 101
Memphis, TN 38141
C101643
Rev 03/2021

PACKAGE LABEL.PRINCIPAL DISPLAY PANEL

NDC 63739-055-65
Gentamicin Sulfate
Cream USP, 0.1%*
Net Wt. 15 grams
Rx Only
FOR EXTERNAL USE ONLY.
NOT FOR OPHTHALMIC USE.

NDC 63739-055-65
Gentamicin Sulfate
Cream USP, 0.1%*
Net Wt. 15 grams
Rx Only
FOR EXTERNAL USE ONLY.
NOT FOR OPHTHALMIC USE.

NDC 63739-055-66
Gentamicin Sulfate
Cream USP, 0.1%*
Net Wt. 30 grams
Rx Only
FOR EXTERNAL USE ONLY.
NOT FOR OPHTHALMIC USE.

NDC 63739-055-66
Gentamicin Sulfate
Cream USP, 0.1%*
Net Wt. 30 grams
Rx Only
FOR EXTERNAL USE ONLY.
NOT FOR OPHTHALMIC USE.